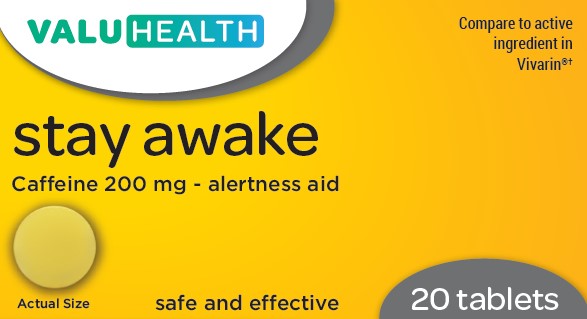 DRUG LABEL: Stay Awake
NDC: 68210-4151 | Form: TABLET
Manufacturer: Spirit Pharmaceuticals LLC
Category: otc | Type: HUMAN OTC DRUG LABEL
Date: 20241211

ACTIVE INGREDIENTS: CAFFEINE 200 mg/1 1
INACTIVE INGREDIENTS: CARNAUBA WAX; CROSCARMELLOSE SODIUM; SILICON DIOXIDE; D&C YELLOW NO. 10 ALUMINUM LAKE; DEXTRATES; ANHYDROUS DIBASIC CALCIUM PHOSPHATE; FD&C RED NO. 40; FD&C YELLOW NO. 6; HYPROMELLOSE, UNSPECIFIED; LACTOSE MONOHYDRATE; MAGNESIUM STEARATE; MICROCRYSTALLINE CELLULOSE; POLYETHYLENE GLYCOL 400; TITANIUM DIOXIDE

Stay Awake (CAFFEINE 200 MG)

Drug Facts

Active ingredient (in each tablet)
Caffeine 200 mg

Purpose

Alertness Aid

Use

■ helps restore mental alertness or wakefulness when experiencing fatigue or drowsiness

Warnings

For occasional use only

Do not use

■ in children under 12 years of age
■ as a substitute for sleep

When using this product limit the use of caffeine containing medications, foods, or beverages because too much caffeine may cause nervousness, irritability, sleeplessness, and occasionally, rapid heartbeat. The recommended dose of this product contains about as much caffeine as a cup of coffee.

Stop use and ask a doctor if fatigue or drowsiness persists or continues to recur

PREGNANCY OR BREAST FEEDING

If pregnant or breast-feeding, ask a health professional before use.

Keep out of reach of children.

OVERDOSAGE

In case of overdose, get medical help or contact a Poison Control Center right away.1(800)222-1222

Directions

■ adults and children 12 years of age and over: take 1 tablet not more often than every 3 to 4 hours.

Other information

■ store at room temperature
■ avoid excessive heat (greater than 100°F) or humidity

INACTIVE INGREDIENT

carnauba wax*,croscarmellose sodium, colloidal silicon
dioxide*, dextrates*, D&C yellow #10 aluminum lake,
dicalcium phosphate*, FD&C red#40 lake*, FD&C yellow
#6 aluminum lake*, hypromellose, lactose*, magnesium
stearate, microcrystalline cellulose, polyethylene glycol,
silicon dioxide*, titanium dioxide
*contains one or more of these ingredients

Questions or comments?

1-888-333-9792

PRINCIPAL DISPLAY PANEL

Stay Awake
Caffeine 200 mg - alertness aid
safe and effective

20 Tablets